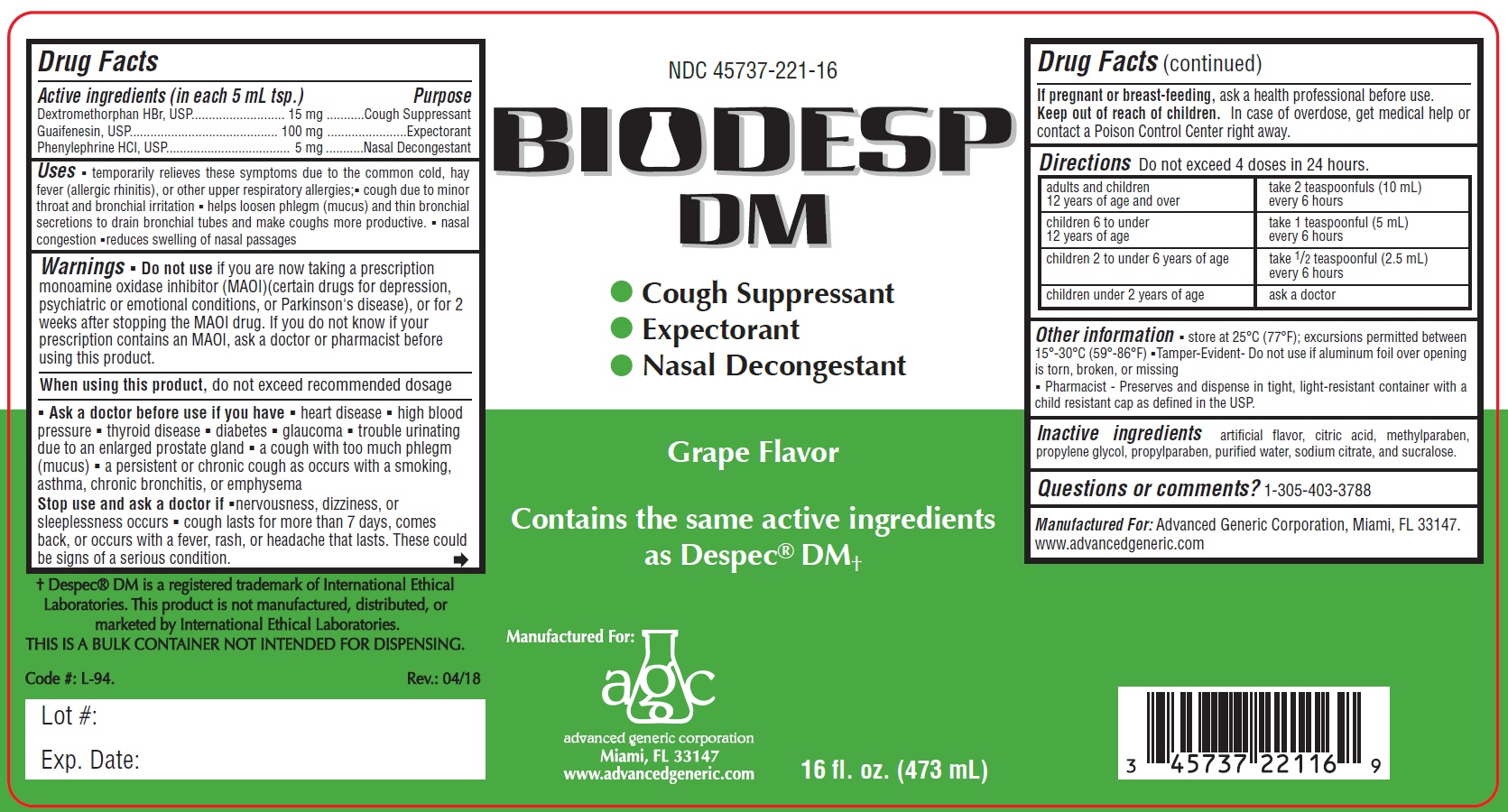 DRUG LABEL: Biodesp
NDC: 45737-221 | Form: LIQUID
Manufacturer: Advanced Generic Corporation
Category: otc | Type: HUMAN OTC DRUG LABEL
Date: 20241220

ACTIVE INGREDIENTS: DEXTROMETHORPHAN HYDROBROMIDE 15 mg/5 mL; GUAIFENESIN 100 mg/5 mL; PHENYLEPHRINE HYDROCHLORIDE 5 mg/5 mL
INACTIVE INGREDIENTS: ANHYDROUS CITRIC ACID; WATER; METHYLPARABEN; PROPYLPARABEN; PROPYLENE GLYCOL; SODIUM CITRATE; SUCRALOSE

AGC-BiodespDM 221

Active Ingredients: (in each 5 mL tsp.) Purpose

Dextromethorphan Hydrobromide 15 mg.................. Cough Suppressant

Guaifenesin 100 mg .............................................. Expectorant
Phenylephrine HCl 5 mg.................................. Decongestant

Purpose

Cough Suppressant

Expectorant

Nasal Decongestant

Uses

- temporarily relieves these symptoms due to the common cold. hay fever (allergic rhinitis), or other upper respiratory allergies;
- cough due to minor throat and bronchial irritation
- helps loosen phlegm (mucus) and thin bronchial secretions to drain bonchial tubes and make coughs more productive
- nasal congestion
- reduces swelling of nasal passages

Warnings

Do not use

If you are now taking a prescription monoamine oxidase inhibitor (MAOI) (certain drugs for depression, psychiatric or emotional conditions or Parkinson’s disease), or for 2 weeks after stopping the MAOI drug. If you do not know if you are taking a prescription drug that contains an MAOI; ask your doctor or pharmacist before taking this product.

When using this product do not exceed recommended dosage

Ask a doctore before use if you have

- heart disease
- high blood pressure
- thyroid disease
- diabetes
- glaucoma
- trouble urinating due to enlarged prostate gland
- a cough with too much phlegm (mucus)
- a persistent or chronic cough as occurs with smoking, asthma, chronic bronchitis or emphysema.

Stop use and ask a doctor if

- nervousness, dizziness, or sleeplessness occurs
- cough lasts for more than 7 days, comes back, or occurs with a fever, rash, or headache that lasts. These could be signs of a serious condition

Keep out of reach of children. In case of overdose, get medical help or contact a Poison Control Center right away.

PREGNANCY OR BREAST FEEDING

If pregnant or breast-feeding,ask a health professional before use.

DOSAGE AND ADMINISTRATION

Directions Do not exceed 4 doses in 24 hours.

adults and children 12 years of age and over | take 2 teaspoonfuls (10 mL) every 6 hours
children 6 to under 12 years of age | take 1 teaspoonful (5 mL) every 6 hours
children 2 to under 6 years of age | take 1/2 teaspoonful (2.5 mL) every 6 hours
children under 2 years of age | ask a doctor

Questions or comments?1-305-403-3788
Manufactured For: Advanced Generic Corporation, Miami, FL 33147.
www.advancedgeneric.com

INACTIVE INGREDIENT

Inactive ingredientsartificial flavor, citric acid, methylparaben, propylene glycol,
propylparaben, purified water, sodium citrate and sucralose.